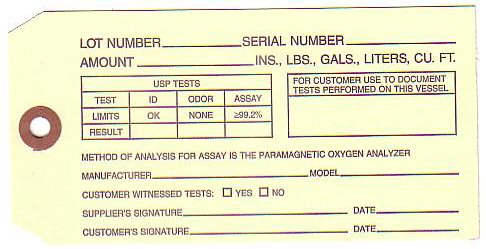 DRUG LABEL: OXYGEN
NDC: 58977-001 | Form: GAS
Manufacturer: Rice Home Medical LLC
Category: prescription | Type: HUMAN PRESCRIPTION DRUG LABEL
Date: 20111201

ACTIVE INGREDIENTS: OXYGEN 99 L/100 L

OXYGEN PURITY TAG

LOT NUMBER____ SERIAL NUMBER________ AMOUNT_____________ INS. LBS GALS LITERS CU FT
USP TESTS
TEST ID ODOR ASSAY
LIMITS OK NONE GREATER THAN OR EQUAL TO 99.2%
RESULTS __ _____ _______
FOR CUSTOMER USE TO DOCUMENT TESTS PERFORMED ON THIS VESSEL
METHOD OF ANALYSIS IS THE PARAMAGNETIC OXYGEN ANALYZER
MANUFACTURER __________ MODEL ________ CUSTOMER WITNESSED TESTS YES__ MO___ SUPPLIERS SIGNATURE _____________ DATE____ CUSTOMER'S SIGNATURE___________ DATE___________
LIQUID OXYGEN DELIVERY TAG THIS VESSEL CONTAINS OXYGEN U.S.P. (SEE REVERSE SIDE FOR TEST RESULTS) OXYGEN PRODUCED BY THE AIR LIQUEFACTION PROCESS - MEDICAL GASES

PRODUCT WARNINGS

THIS VESSEL CONTAINS OXYGEN U.S.P. (SEE REVERSE SIDE FOR TEST RESULTS) OXYGEN PRODUCED BY THE AIR LIQUEFACTION PROCESS.